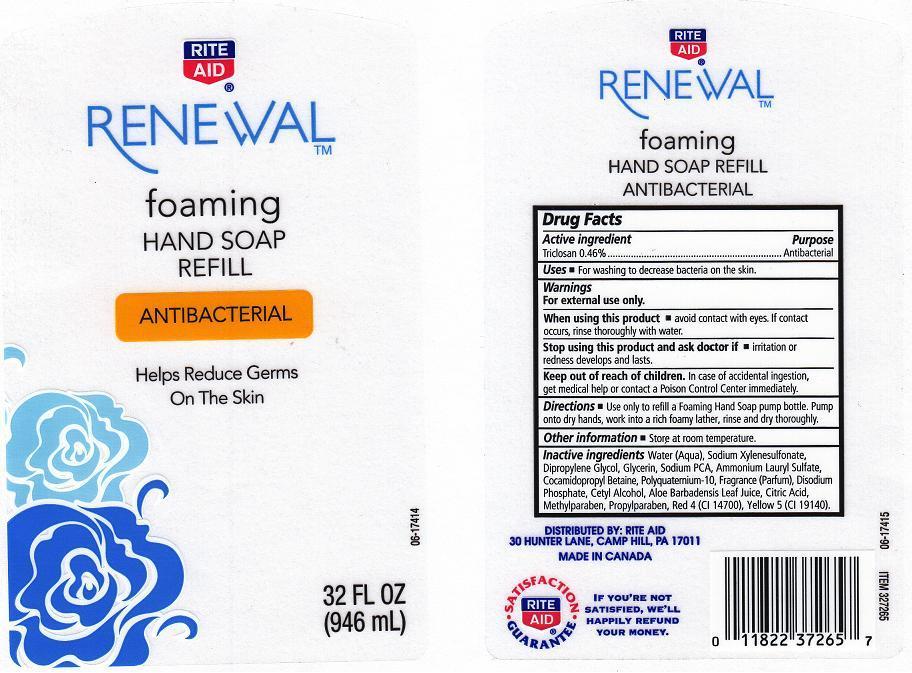 DRUG LABEL: RITE AID RENEWAL
NDC: 11822-1773 | Form: LIQUID
Manufacturer: RITE AID CORPORATION
Category: otc | Type: HUMAN OTC DRUG LABEL
Date: 20120821

ACTIVE INGREDIENTS: TRICLOSAN 0.46 mg/100 mL
INACTIVE INGREDIENTS: WATER; SODIUM XYLENESULFONATE; DIPROPYLENE GLYCOL; GLYCERIN; SODIUM PYRROLIDONE CARBOXYLATE; AMMONIUM LAURYL SULFATE; COCAMIDOPROPYL BETAINE; POLYQUATERNIUM-10 (400 CPS AT 2%); SODIUM PHOSPHATE, DIBASIC; CETYL ALCOHOL; ALOE VERA LEAF; CITRIC ACID MONOHYDRATE; METHYLPARABEN; PROPYLPARABEN; FD&C RED NO. 4; FD&C YELLOW NO. 5

DRUG FACTS

ACTIVE INGREDIENT

TRICLOSAN 0.46%

PURPOSE

ANTIBACTERIAL

USES

FOR WASHING TO DECREASE BACTERIA ON THE SKIN.

WARNINGS

FOR EXTERNAL USE ONLY.

WHEN USING THIS PRODUCT

AVOID CONTACT WITH EYES. IF CONTACT OCCURS, RINSE THOROUGHLY WITH WATER.

STOP USING THIS PRODUCT AND ASK DOCTOR IF

IRRITATION OR REDNESS DEVELOPS AND LASTS.

KEEP OUT OF REACH OF CHILDREN

IN CASE OF ACCIDENTAL INGESTION, GET MEDICAL HELP OR CONTACT A POISON CONTROL CENTER IMMEDIATELY.

DIRECTIONS

USE ONLY TO REFILL A FOAMING HAND SOAP PUMP BOTTLE. PUMP ONTO DRY HANDS, WORK INTO A RICH FOAMY LATHER, RINSE AND DRY THOROUGHLY.

OTHER INFORMATION

STORE AT ROOM TEMPERATURE.

INACTIVE INGREDIENTS

WATER (AQUA), SODIUM XYLENESULFONATE, DIPROPYLENE GLYCOL, GLYCERIN, SODIUM PCA, AMMONIUM LAURYL SULFATE, COCAMIDOPROPYL BETAINE, POLYQUATERNIUM-10, FRAGRANCE (PARFUM), DISODIUM PHOSPHATE, CETYL ALCOHOL, ALOE BARBADENSIS LEAF JUICE, CITRIC ACID, METHYLPARABEN, PROPYLPARABEN, RED 4 (CI 14700), YELLOW 5 (CI 19140).